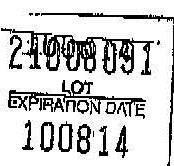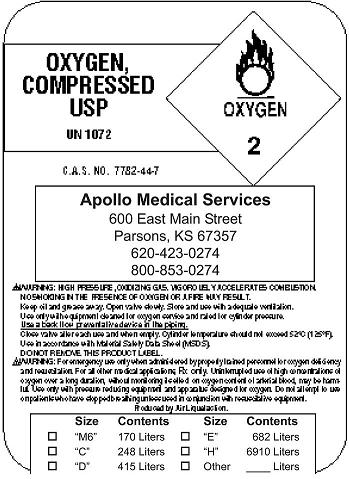 DRUG LABEL: Oxygen
NDC: 24781-0001 | Form: GAS
Manufacturer: Apollo Services Inc.
Category: prescription | Type: HUMAN PRESCRIPTION DRUG LABEL
Date: 20091009

ACTIVE INGREDIENTS: Oxygen 99 L/100 L

Oxygen